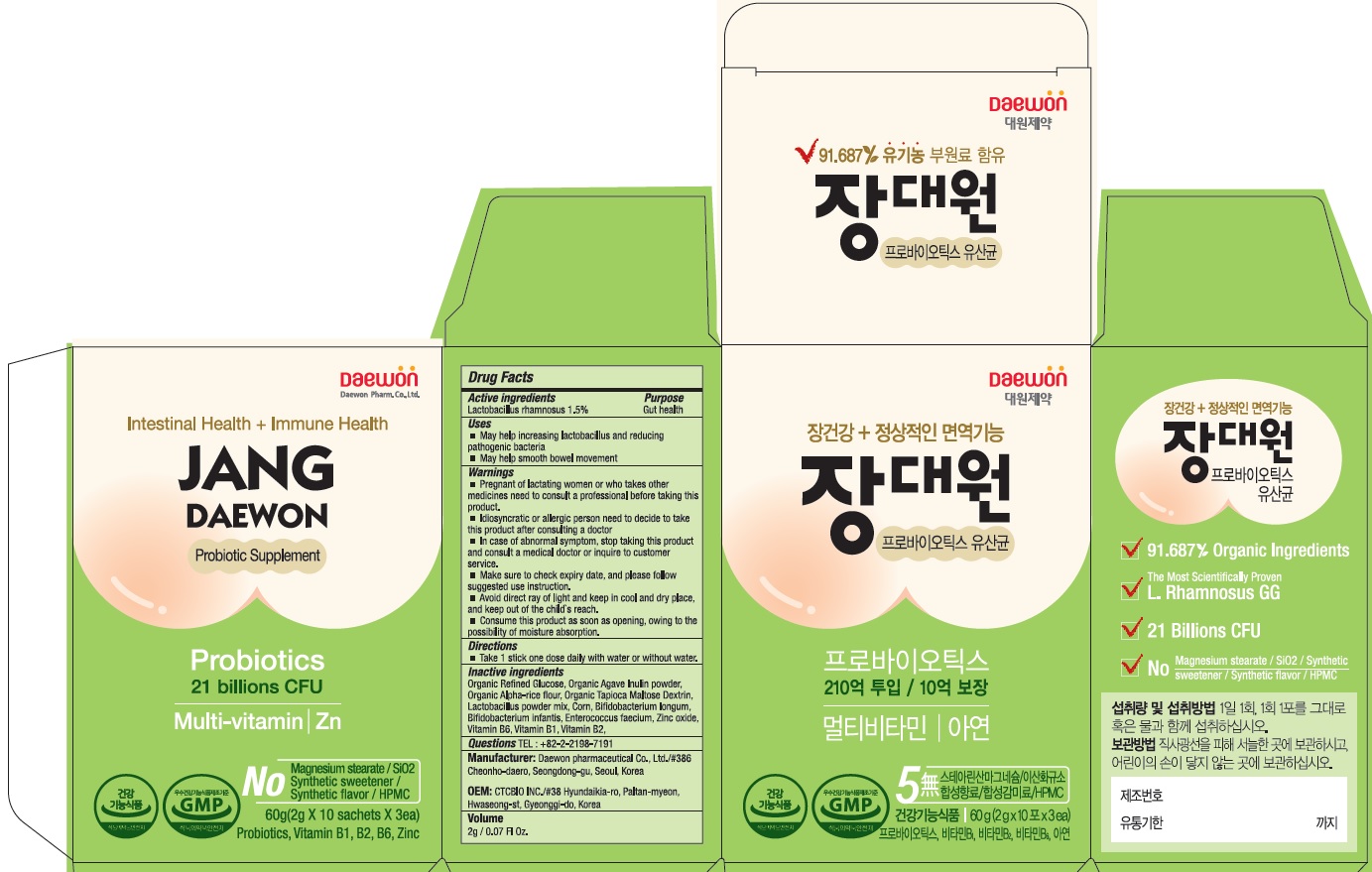 DRUG LABEL: Jangdaewon Probiotics
NDC: 72460-600 | Form: POWDER
Manufacturer: Daewon Pharmaceutical Co., Ltd.
Category: otc | Type: HUMAN OTC DRUG LABEL
Date: 20190313

ACTIVE INGREDIENTS: Lactobacillus rhamnosus 30 mg/2 g
INACTIVE INGREDIENTS: Bifidobacterium longum

ACTIVE INGREDIENT

Active ingredients: Lactobacillus rhamnosus 1.5%

INACTIVE INGREDIENT

Inactive ingredients:

Organic Refined Glucose, Organic Agave Inulin powder, Organic Alpha-rice flour, Organic Tapioca Maltose Dextrin, Lactobacillus powder mix, Corn, Bifidobacterium longum, Bifidobacterium infantis, Enterococcus faecium, Zinc oxide, Vitamin B6, Vitamin B1, Vitamin B2

PURPOSE

Purpose: Gut health

WARNINGS

■ Pregnant of lactating women or who takes other medicines need to consult a professional before taking this product.
■ Idiosyncratic or allergic person need to decide to take this product after consulting a doctor
■ In case of abnormal symptom, stop taking this product and consult a medical doctor or inquire to customer service.
■ Make sure to check expiry date, and please follow suggested use instruction.
■ Avoid direct ray of light and keep in cool and dry place, and keep out of the child's reach.
■ Consume this product as soon as opening, owing to the possibility of moisture absorption.

KEEP OUT OF REACH OF CHILDREN

Keep out of the child's reach.

Uses

■ May help increasing lactobacillus and reducing pathogenic bacteria
■ May help smooth bowel movement

Directions

■ Take 1 stick one dose daily with water or without water.